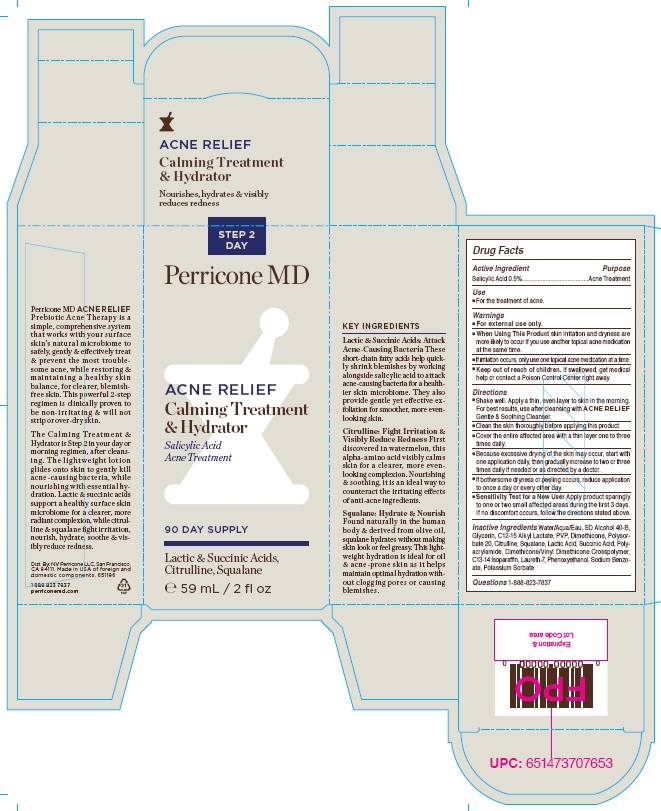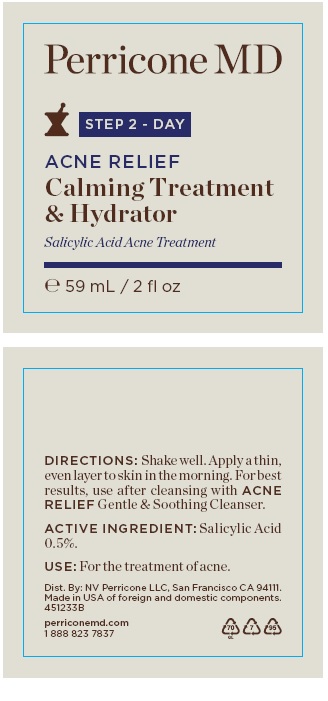 DRUG LABEL: ACNE RELIEF CALMING TREATMENT AND HYDRATOR
NDC: 45634-102 | Form: LOTION
Manufacturer: NV Perricone LLC
Category: otc | Type: HUMAN OTC DRUG LABEL
Date: 20220210

ACTIVE INGREDIENTS: SALICYLIC ACID 0.295 g/59 mL
INACTIVE INGREDIENTS: WATER; ALCOHOL; GLYCERIN; C12-15 ALKYL LACTATE; POVIDONE, UNSPECIFIED; DIMETHICONE; POLYSORBATE 20; CITRULLINE; SQUALANE; LACTIC ACID; SUCCINIC ACID; POLYACRYLAMIDE (10000 MW); DIMETHICONE/VINYL DIMETHICONE CROSSPOLYMER (HARD PARTICLE); C13-14 ISOPARAFFIN; LAURETH-7; PHENOXYETHANOL; SODIUM BENZOATE; POTASSIUM SORBATE

ACNE RELIEF CALMING TREATMENT & HYDRATOR STEP 2 - DAY

Drug Facts

Active Ingredient
Salicylic Acid 0.5%

Purpose
Acne Treatment

Use
■ For the treatment of acne.

Warnings
■ For external use only.
■ When Using This Product Skin irritation and dryness are
more likely to occur if you use another topical acne medication
at the same time.
■ If irritation occurs, only use one topical acne medication at a time.
■ Keep out of reach of children. If swallowed, get medical
help or contact a Poison Control Center right away.

Directions
■ Shake well. Apply a thin, even layer to skin in the morning.
For best results, use after cleansing with ACNE RELIEF
Gentle & Soothing Cleanser.
■ Clean the skin thoroughly before applying this product.
■ Cover the entire affected area with a thin layer one to three
times daily.
■ Because excessive drying of the skin may occur, start with
one application daily, then gradually increase to two or three
times daily if needed or as directed by a doctor.
■ If bothersome dryness or peeling occurs, reduce application
to once a day or every other day.
■ Sensitivity Test for a New User Apply product sparingly
to one or two small affected areas during the first 3 days.
If no discomfort occurs, follow the directions stated above.

INACTIVE INGREDIENT

Inactive Ingredients Water/Aqua/Eau, SD Alcohol 40-B,
Glycerin, C12-15 Alkyl Lactate, PVP, Dimethicone, Polysor-
bate 20, Citrulline, Squalane, Lactic Acid, Succinic Acid, Poly-
acrylamide, Dimethicone/Vinyl Dimethicone Crosspolymer,
C13-14 Isoparaffin, Laureth-7, Phenoxyethanol, Sodium Benzo-
atr, Potassium Sorbate

Questions 1-888-823-7837

Product Package

ACNE RELIEF

Calming Treatment
& Hydrator

Nourishes, hydrates & visibly
reduces redness

STEP 2
DAY

Perricone MD

ACNE RELIEF

90 DAY SUPPLY

Lactic & Succinic Acids,
Citrulline, Squalane

℮ 59 mL / 2 fl oz

KEY INGREDIENTS
Lactic & Succinic Acids: Attack
Acne-Causing Bacteria These
short-chain fatty acids help quickly
shrink blemishes by working
alongside salicylic acid to attack
acne-causing bacteria for a healthier
skin microbiome. They also
provide gentle yet effective ex-
foliation for smoother, more even=
looking skin.

Citrulline: Fight Irritation &
Visibly Reduce Redness First
discovered in watermelon, this
alpha-amino acid visibly calms
skin for a clearer, more even-
looking complexion. Nourishing
& soothing, it is an ideal way to
counteract the irritating effects
of anti-acne ingredients.

Squalane: Hydrate & Nourish
Found naturally in the human
body & derived from olive oil,
squalane hydrates without making
skin look or feel greasy. This lightweight
hydration is ideal for oil
& acne-prone skin as it helps
maintain optimal hydration without
clogging pores or causing
blemishes.

Perricone MD ACNE RELIEF
Prebiotic Acne Therapy is a
simple, comprehensive system
that works with your surface
skin’s natural microbiome to
safely, gently & effectively treat
& prevent the most troublesome
acne, while restoring &
maintaining a healthy skin
balance, for clearer, blemish-
free skin. This powerful 2-step
regimen is clinically proven to
be non-irritating & will not
strip or over-dry skin.

The Calming Treatment &
Hydrator is Step 2 in your day or
morning regimen, after cleans-
ing, The lightweight lotion
glides onto skin to gently kill
acne-causing bacteria, while
nourishing with essential hy-
dration. Lactic & succinic acids
support a healthy surface skin
microbiome for a clearer, more
radiant complexion, while citrul-
line & squalane fight irritation,
nourish, hydrate, soothe & vis-
ibly reduce redness.

Dist. By: NV Perricone LLC, San Francisco,
CA 94111. Made in USA of foreign and
domestic components. 651196

1 888 823 7837
perriconemd.com

Expiration &
Lot Code area

Outer Box

Bottle

rege